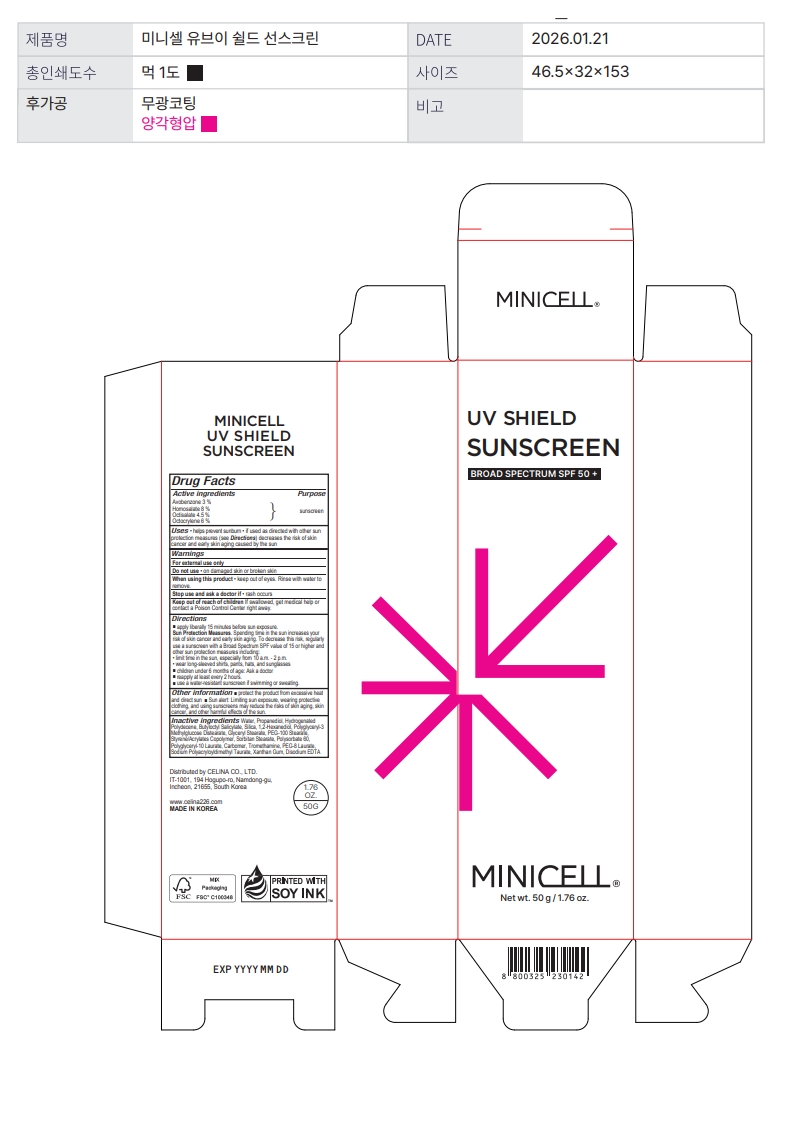 DRUG LABEL: MINICELL UV SHIELD SUNSCREEN
NDC: 87287-150 | Form: CREAM
Manufacturer: CELINA CO., LTD.
Category: otc | Type: HUMAN OTC DRUG LABEL
Date: 20260121

ACTIVE INGREDIENTS: OCTOCRYLENE 3 g/50 g; AVOBENZONE 1.5 g/50 g; OCTISALATE 2.25 g/50 g; HOMOSALATE 4 g/50 g
INACTIVE INGREDIENTS: SILICON DIOXIDE; POLYGLYCERYL-3 METHYLGLUCOSE DISTEARATE; POLYSORBATE 60; POLYGLYCERYL-10 LAURATE; GLYCERYL STEARATE; PEG-100 STEARATE; SORBITAN STEARATE; PROPANEDIOL; 1,2-HEXANEDIOL; TROMETHAMINE; EDETATE DISODIUM ANHYDROUS; PEG-8 LAURATE; BUTYLOCTYL SALICYLATE; WATER; CARBOMER; SODIUM POLYACRYLOYLDIMETHYL TAURATE; XANTHAN GUM

Actiove ingredients

AVOBENZONE, HOMOSALATE, OCTISALATE, OCTOCRYLENE

Purpose

SUNSCREEN

Uses

helps prevent sunburn • if used as directed with other sun

protection measures (see Directions) decreases the risk of skin

cancer and early skin aging caused by the sun

Warnings

For external use only

Do not use

• on damaged skin or broken skin

When using this product

• keep out of eyes. Rinse with water to remove.

Stop use

and ask a doctor if • rash occurs

Keep out of reach

of children If swallowed, get medical help or contact a Poison Control Center right away.

Directions

■ apply liberally 15 minutes before sun exposure.

Sun Protection Measures. Spending time in the sun increases your risk of skin cancer and early skin aging. To decrease this risk, regularly use a sunscreen with a Broad Spectrum SPF value of 15 or higher and other sun protection measures including:

• limit time in the sun, especially from 10 a.m. - 2 p.m.

• wear long-sleeved shirts, pants, hats, and sunglasses

■ children under 6 months of age: Ask a doctor

■ reapply at least every 2 hours

■ use a water-resistant sunscreen if swimming or sweating

Other information

■ protect the product from excessive heat and direct sun ■ Sun alert: Limiting sun exposure, wearing protective clothing, and using sunscreens may reduce the risks of skin aging, skin cancer, and other harmful effects of the sun.

Inactive ingredients

Water, Propanediol, Butyloctyl Salicylate, Silica, Hydrogenated Polydecene, 1,2-Hexanediol, Polyglyceryl-3 Methylglucose Distearate, Glyceryl Stearate, PEG-100 Stearate, Styrene/Acrylates Copolymer, Sorbitan Stearate, Polysorbate 60, Polyglyceryl-10 Laurate, Carbomer, Tromethamine, PEG-8 Laurate, Sodium Polyacryloyldimethyl Taurate, Xanthan Gum, Disodium EDTA